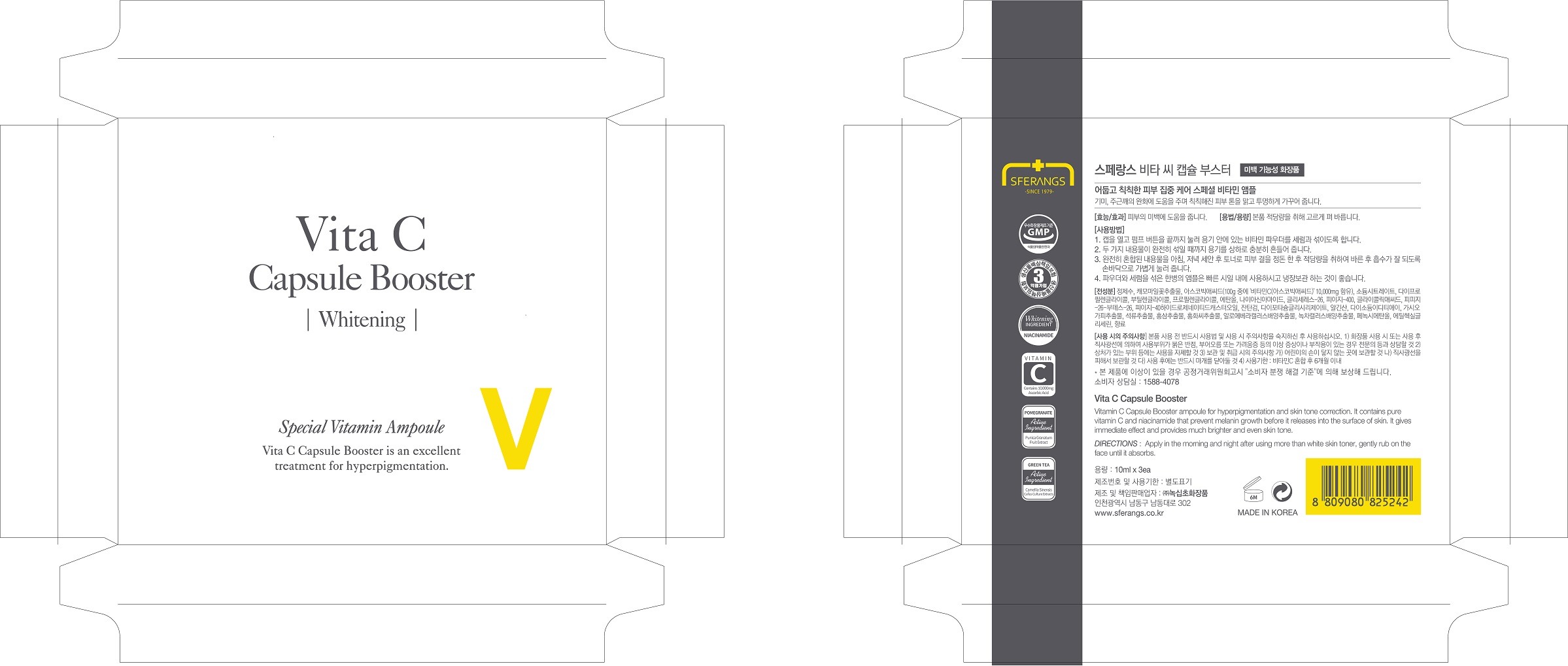 DRUG LABEL: SFERANGS VITA C CAPSULEBOOSTER
NDC: 73590-0041 | Form: LIQUID
Manufacturer: NOKSIBCHO cosmetic Co., Ltd.
Category: otc | Type: HUMAN OTC DRUG LABEL
Date: 20200331

ACTIVE INGREDIENTS: NIACINAMIDE 2 g/100 mL
INACTIVE INGREDIENTS: WATER

Drug Facts

ACTIVE INGREDIENT

niacinamide

INACTIVE INGREDIENT

Water
Anthemis Nobilis Flower Extract
Ascorbic Acid
Sodium Citrate
Dipropylene Glycol
Butylene glycol
Propylene Glycol
Alcohol
Glycereth-26
PEG-400
Glycolic acid
PPG-26-Buteth-26
PEG-40 Hydrogenated Castor Oil
Xanthan GUM
Dipotassium Glycyrrhizate
Algin
Disodium EDTA
Acanthopanax Senticosus (Eleuthero) Root Extract
Punica Granatum Fruit Extract
Panax Ginseng Root Extract
Carthamus Tinctorius (Safflower) Flower Extract
Aloe vera Callus Culture extracts
Camellia sinensis Callus Culture extracts
Phenoxyethanol
Ethylhexylglycerin
Parfum

PURPOSE

anti-wrinkle

keep out of reach of the children

INDICATIONS AND USAGE

apply proper amount to the skin

WARNINGS

For external use only
When using this product

■ if the following symptoms occurs after use, stop use and consult with a skin specialist

red specks, swelling, itching

■ don’t use on the part where there is injury, eczema, or dermatitis

Keep out of reach of children

■ if swallowed, get medical help or contact a person control center immediately